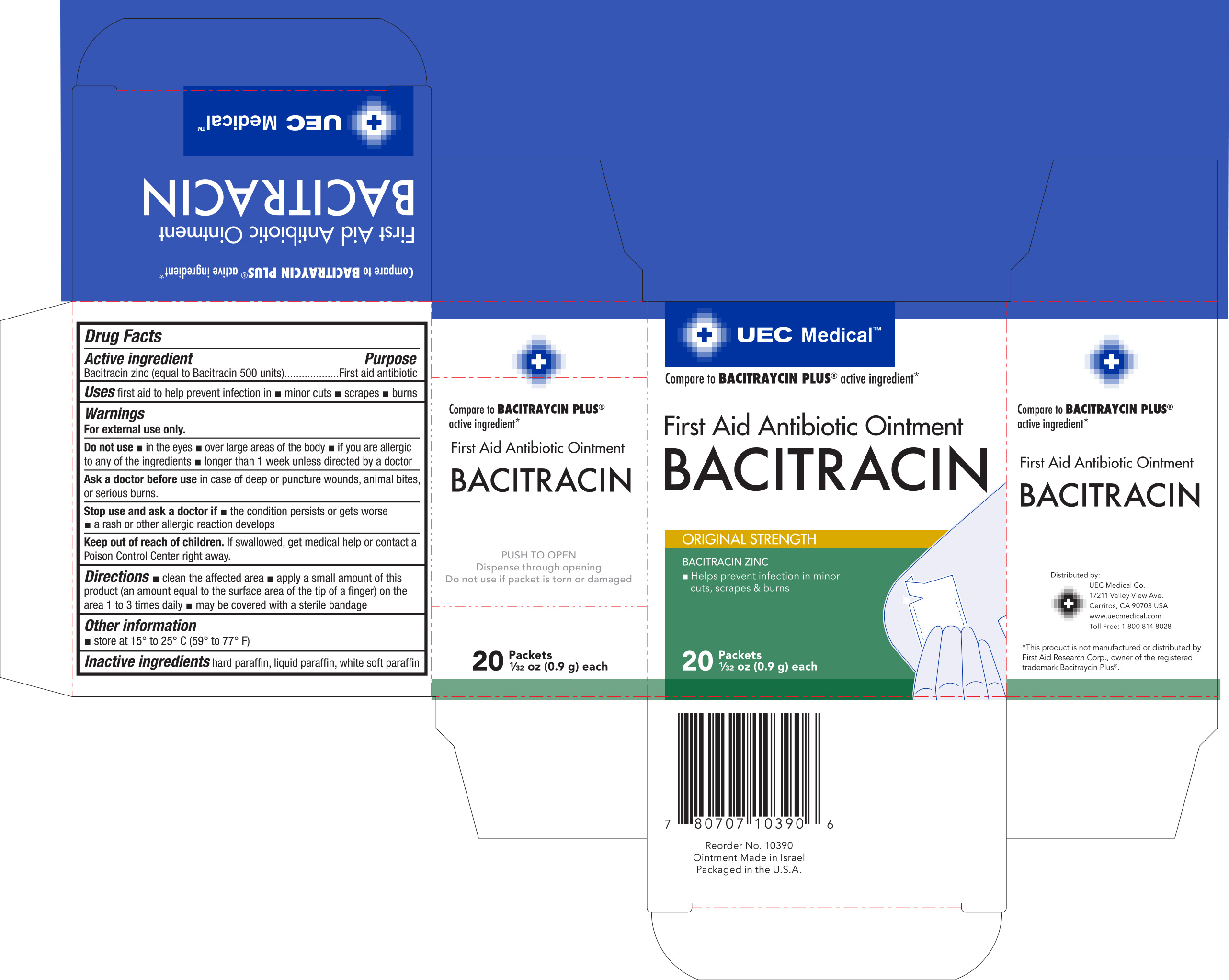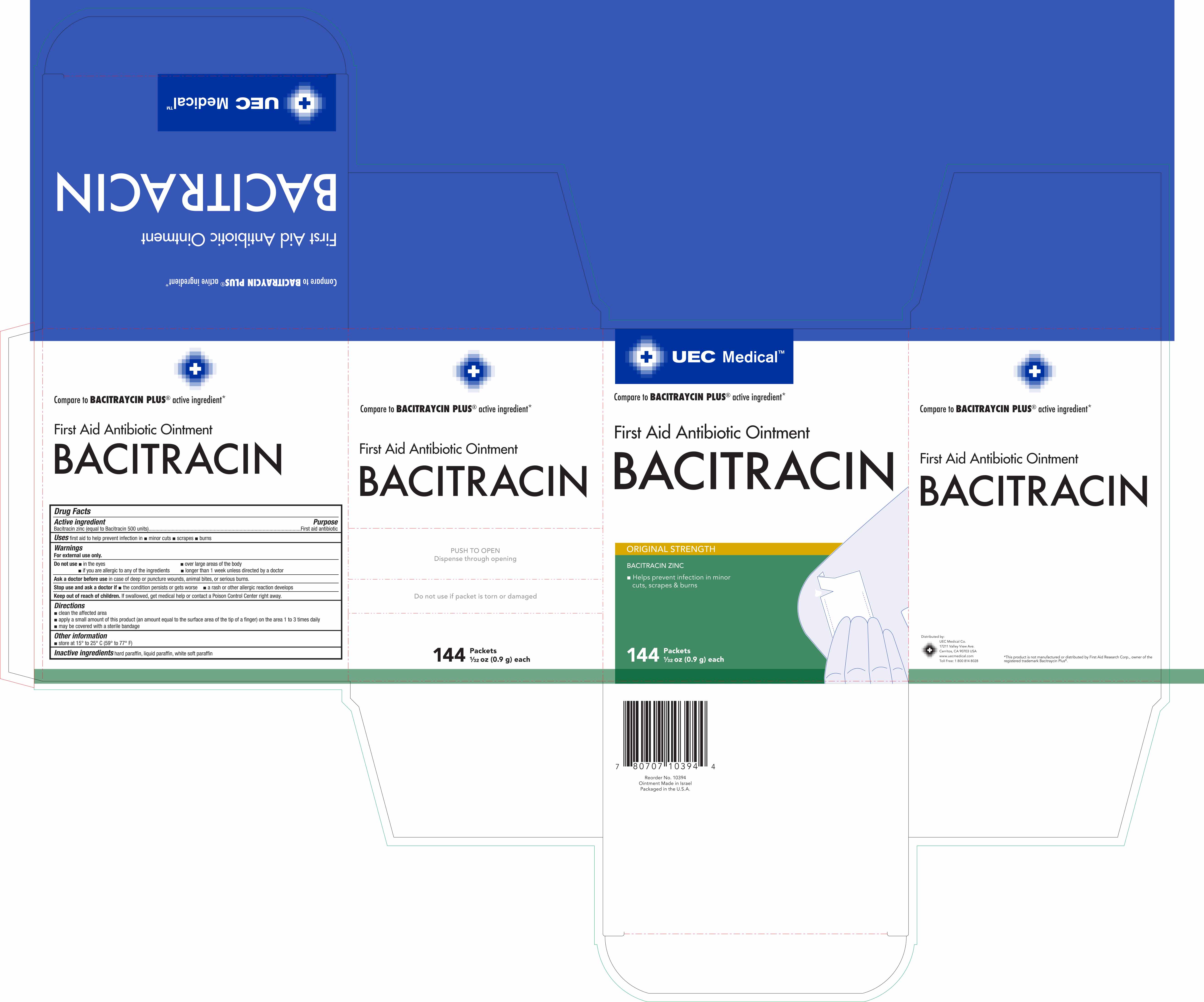 DRUG LABEL: UEC Medical First Aid Antibiotic
NDC: 65923-390 | Form: OINTMENT
Manufacturer: United Exchange Corp.
Category: otc | Type: HUMAN OTC DRUG LABEL
Date: 20180405

ACTIVE INGREDIENTS: BACITRACIN ZINC 500 [iU]/1 g
INACTIVE INGREDIENTS: PARAFFIN; MINERAL OIL

UEC Medical Antibiotic Ointment 0.9g NBE Bacitraycin 20 and 144 ct- 10393 and 10394 (2018)

Active ingredient Purpose

Bacitracin zinc (equal to Bacitracin 500 units)..........................First aid antibiotic

PURPOSE

Uses first aid to help prevent infection in

- minor cuts
- scrapes
- burns

Warnings

For external use only

Do not use

- in the eyes
- over large areas of the body
- if you are allergic to any of the ingredients
- longer than 1 week unless directed by a doctor

Ask a doctor before use in case of deep or puncture wounds, animal bites, or serious burns

Stop use and ask a doctor if

- the condition persists or gets worse
- a rash or other allergic reaction develops

Keep out of reach of children. If swallowed, get medical help or contact a Poison Control Center right away.

Directions

- clean the affected area
- apply a small amount of this product (an amount equal to the surface area of the tip of a finger) on the area 1 to 3 times daily
- may be covered with a sterile bandage

Other information

- store at 15° to 25° C (59° to 77° F)

INACTIVE INGREDIENT

Inactive ingredients hard paraffin, liquid paraffin, white soft paraffin

DOSAGE AND ADMINISTRATION

Distributed by:

UEC Medical

17211 Valley View Ave.

Cerritos, CA 90703 USA